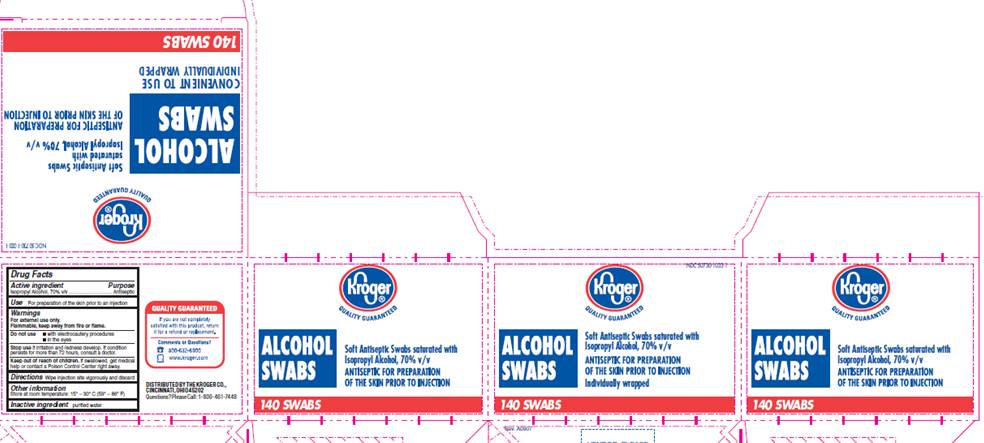 DRUG LABEL: Isopropyl alcohol Prep Pad
NDC: 50730-1033 | Form: SWAB
Manufacturer: H and P Industries, Inc. dba Triad Group
Category: otc | Type: HUMAN OTC DRUG LABEL
Date: 20091214

ACTIVE INGREDIENTS: Isopropyl alcohol .7 mL/1 1
INACTIVE INGREDIENTS: water

DRUG FACTS

ACTIVE INGREDIENT

Isopropyl Alcohol 70% v/v

PURPOSE

Antiseptic

USE

For preparation of the skin prior to an injection

WARNINGS

For external use only.
Flammable, keep away from fire or flame.

Do not use

- with electrocautery procedures
- in the eyes

Stop use

if irritation and redness develop. If condition persists for more than 72 hours, consult a doctor.

Keep out of reach of children

If swallowed, get medical help or contact a Poison Control Center right away.

DIRECTIONS

Wipe injection site vigorously and discard

OTHER INFORMATION

Store at room temperature 15° - 30° C (59° - 86° F)

INACTIVE INGREDIENT

purified water

PACKAGE INFORMATION

NDC 50730-1033-1
Kroeger®
Quality Guaranteed
ALCOHOL SWABS
Soft Antiseptic Swabs saturated with
Isopropyl Alcohol, 70% v/v
ANTISEPTIC FOR PREPARATION OF THE SKIN PRIOR TO INJECTION
Individually wrapped
140 SWABS
Quality Guaranteed
If you are not completely satisfied with this product, return it for a refund or replacement.
Comments or Questions?
800-632-6900
www.kroeger.com
DISTRIBUTED BY THE KROEGER CO.,
CINCINNATI, OHIO 45202
Questions? Please Call: 1-800-491-7448